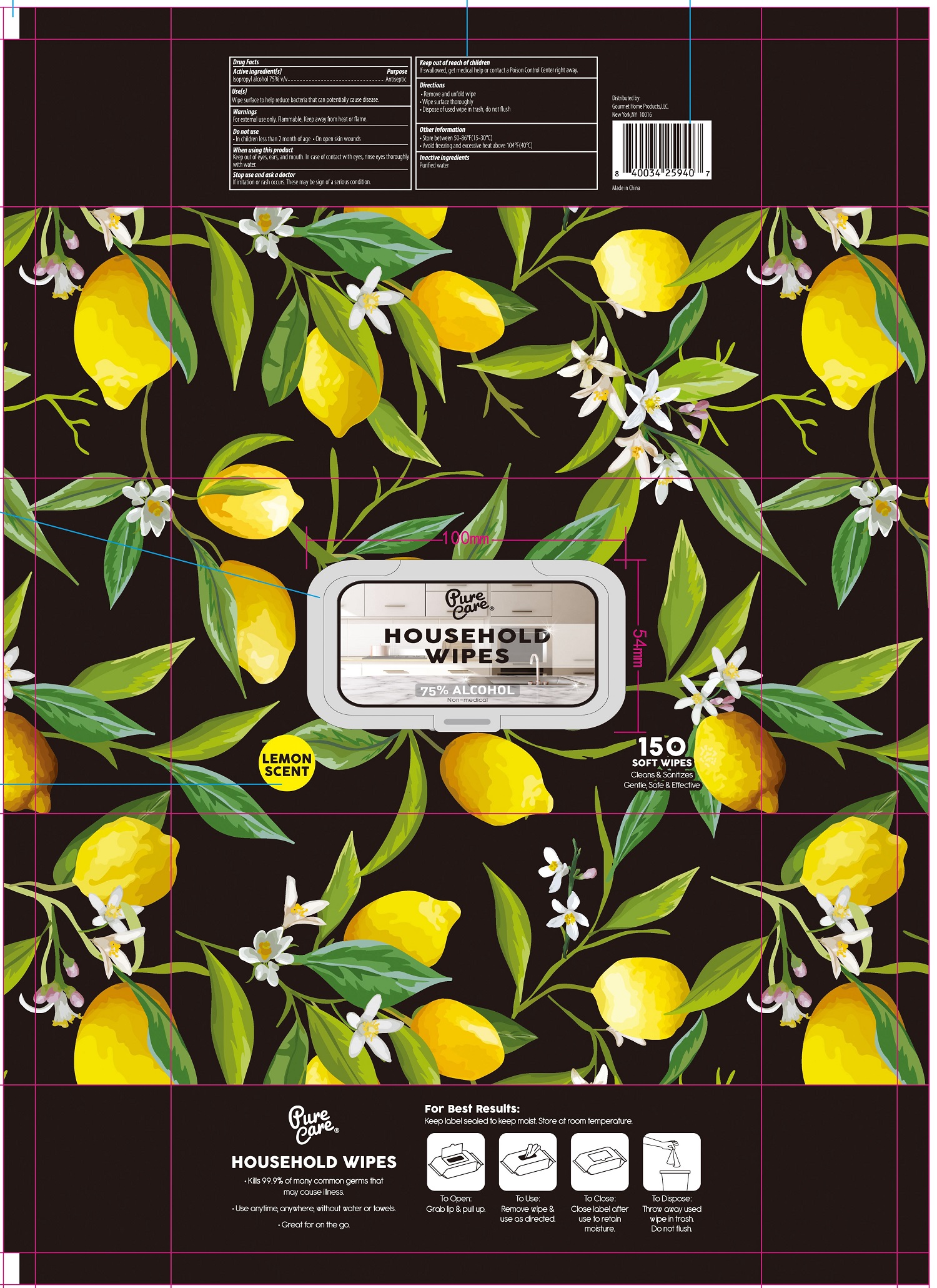 DRUG LABEL: Pure Care Household Wipes
NDC: 78536-008 | Form: CLOTH
Manufacturer: Zhejiang Yiwu Mingou Biotechnology Co., Ltd.
Category: otc | Type: HUMAN OTC DRUG LABEL
Date: 20201212

ACTIVE INGREDIENTS: ISOPROPYL ALCOHOL 75 mL/100 mL
INACTIVE INGREDIENTS: WATER

78536-008 75% Isopropyl Pure Care Household Wipes

ACTIVE INGREDIENT

Isopropyl Alcohol 75%

PURPOSE

Antiseptic

USE

Wipe surface to help reduce bacteria that can potentially cause disease.

Warning

For external use only. Flammable,Keep away from heat or flame.
Do not use
·in children less than 2 month of age·On open skin wounds
When using this product
Keep out of eyes, ears, and mouth. In case of contact with eyes, rinse eyes thoroughly
with water.
Stop use and ask a doctor
lf irritation or rash occurs. These may be sign of a serious condition.

KEEP OUT OF REACH OF CHILDREN

lf swallowed, get medical help or contact a Poison Control Center right away.

Directions

-Remove and unfold wipe
·Wipe surface thoroughly
·Dispose of used wipe in trash, do not flush

Inactive ingredients

Purified water